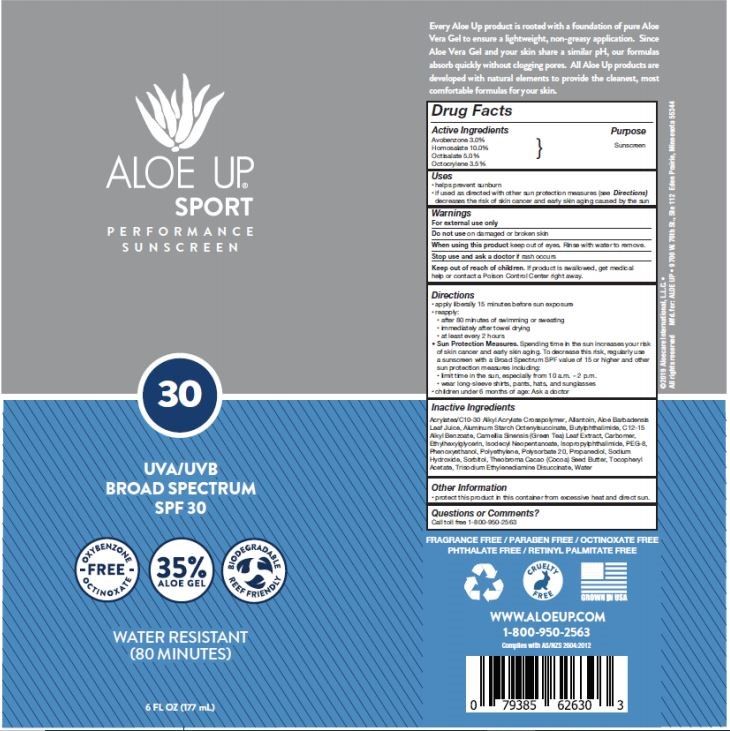 DRUG LABEL: ALOE UP
NDC: 58443-0326 | Form: SPRAY
Manufacturer: Prime Enterprises Inc.
Category: otc | Type: HUMAN OTC DRUG LABEL
Date: 20200512

ACTIVE INGREDIENTS: HOMOSALATE 100 mg/1 mL; OCTOCRYLENE 35 mg/1 mL; AVOBENZONE 30 mg/1 mL; OCTISALATE 50 mg/1 mL
INACTIVE INGREDIENTS: ALUMINUM STARCH OCTENYLSUCCINATE; ISOPROPYLPHTHALIMIDE; SORBITOL; PROPANEDIOL; TRISODIUM ETHYLENEDIAMINE DISUCCINATE; CARBOMER HOMOPOLYMER, UNSPECIFIED TYPE; POLYETHYLENE GLYCOL 400; COCOA BUTTER; ISODECYL NEOPENTANOATE; HIGH DENSITY POLYETHYLENE; ALLANTOIN; PHENOXYETHANOL; CARBOMER INTERPOLYMER TYPE A (55000 CPS); ALKYL (C12-15) BENZOATE; POLYSORBATE 20; ALPHA-TOCOPHEROL ACETATE; WATER; ALOE VERA LEAF; N-BUTYLPHTHALIMIDE; CAMELLIA SINENSIS FLOWER; SODIUM HYDROXIDE; ETHYLHEXYLGLYCERIN

ALOE UP SPORT PERFORMANCE SUNSCREEN Spectrum SPF 30

INACTIVE INGREDIENTS

Acrylates/C10-30 Alkyl Acrylate Crosspolymer, Allantoin, Aloe Barbadensis Leaf Juice, Aluminum Starch Octenylsuccinate, Butylphthalimide, C12-15 Alkyl Benzoate, Camellia Sinensis (Green Tea) Leaf Extract, Carbomer, Iodopropynyl Butylcarbamate, Isodecyl Neopentanoate, Isopropylphthalimide, PEG-8, Phenoxyethanol, Polyethylene, Polysorbate 20, Propanediol, Sorbitol, Theobroma Cacao (Cocoa) Seed Butter, Tocopheryl Acetate, Triethanolamine, Trisodium Ethylenediamine Disuccinate, Water

Warnings

For external use only

Do not use on damaged or broken skin.

When using this product keep out of eyes. Rinse with water to remove. Keep away from face to avoid breathing it.

Stop use and ask a doctor if rash occurs.

Keep out of reach of children. If product is swallowed, get medical help or contact a Poison Control Center right away.

Do not use on damaged or broken skin

When using this product keep out of eyes. Rinse with water to remove.

Stop use and ask a doctor if rash occurs

Keep out of reach of children. If product is swallowed, get medical help or contact a Poison Control Center right away.

Purpose

Sunscreen

Uses

- helps prevent sunburn
  - if used as directed with other sun protection measures (see Directions) decreases the risk of skin cancer and early skin aging caused by the sun

Active Ingredients

Avobenzone 3.0%

Octocrylene 3.5%

Homosalate 10.0%

Octisalate 5.0%

Directions

- apply liberally 15 minutes before sun exposure
- reapply:
- after 80 minutes of swimming or sweating
- immediately after towel drying
- at least every 2 hours
- Sun Protection Measures Spending time ine the sun increases your risk of skin cancer and early skin aging. To decrease this risk, regularly use a sunscreen with a broad spectrum SPF valvue of 15 or higher and other sun protecion measures including:
- limit tim ein the sun, especially from 10am-2pm
- wear long sleeve shirts, pants, hats, and sunglasses
- children under 6 months: Ask a doctor

Other Information

- protect this product from excesive heat and direct sun

Questions or Comments?

Call Toll free 1-855-950-2563